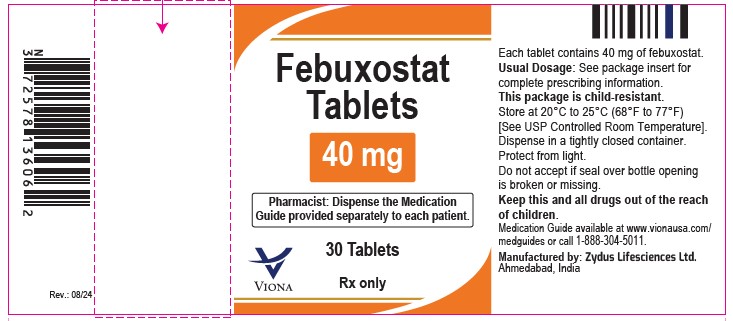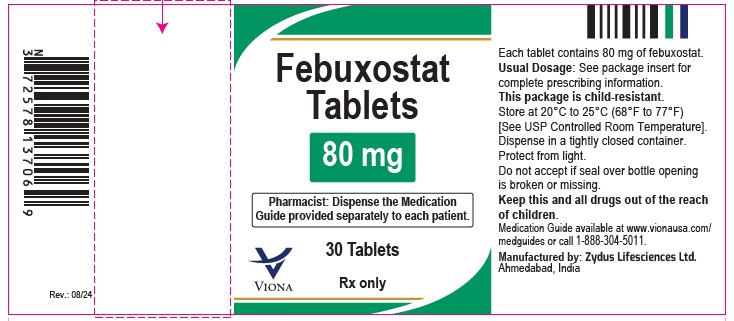 DRUG LABEL: febuxostat
NDC: 70771-1552 | Form: TABLET
Manufacturer: Zydus Lifesciences Limited
Category: prescription | Type: HUMAN PRESCRIPTION DRUG LABEL
Date: 20240816

ACTIVE INGREDIENTS: FEBUXOSTAT 40 mg/1 1
INACTIVE INGREDIENTS: SILICON DIOXIDE; CROSCARMELLOSE SODIUM; HYPROMELLOSES; LACTOSE MONOHYDRATE; CELLULOSE, MICROCRYSTALLINE; POLYETHYLENE GLYCOL, UNSPECIFIED; POVIDONE; SODIUM STEARYL FUMARATE; TALC; TITANIUM DIOXIDE

Febuxostat Tablets

PACKAGE LABEL.PRINCIPAL DISPLAY PANEL

Febuxostat Tablets, 40 mg – 30's count

NDC- 70771-1552-3

Febuxostat Tablets, 80 mg – 30's count

NDC- 70771-1553-3